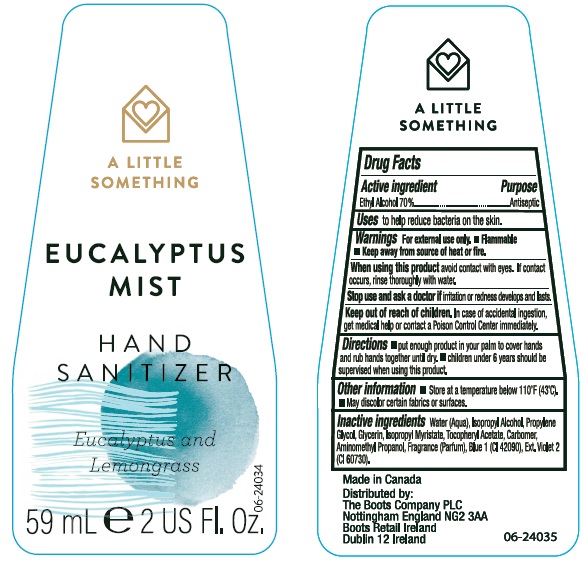 DRUG LABEL: A Little Something Eucalyptus Mist Hand Sanitier
NDC: 0363-1050 | Form: LIQUID
Manufacturer: Walgreen Company
Category: otc | Type: HUMAN OTC DRUG LABEL
Date: 20190529

ACTIVE INGREDIENTS: ALCOHOL 700 mg/1 mL
INACTIVE INGREDIENTS: WATER; ISOPROPYL ALCOHOL; PROPYLENE GLYCOL; GLYCERIN; ISOPROPYL MYRISTATE; .ALPHA.-TOCOPHEROL ACETATE, DL-; CARBOMER 934; AMINOMETHYLPROPANOL; FD&C BLUE NO. 1; EXT. D&C VIOLET NO. 2

Image of the label